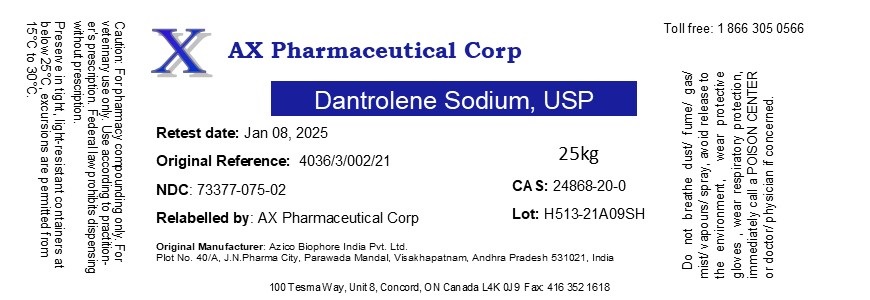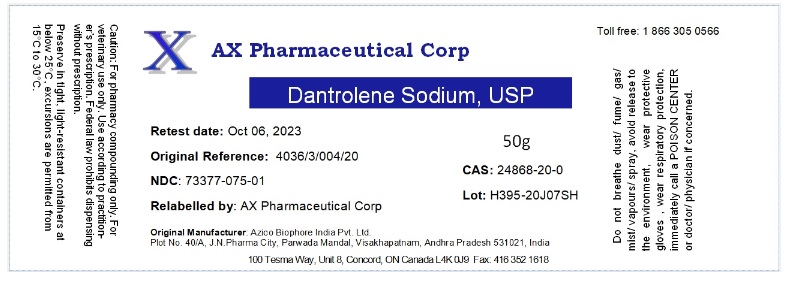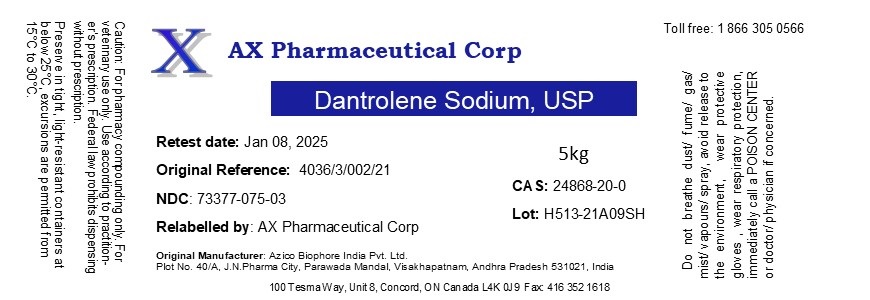 DRUG LABEL: Dantrolene Sodium
NDC: 73377-075 | Form: POWDER
Manufacturer: AX Pharmaceutical Corp
Category: other | Type: BULK INGREDIENT - ANIMAL DRUG
Date: 20230103

ACTIVE INGREDIENTS: DANTROLENE SODIUM 1 g/1 g

Dantrolene Sodium